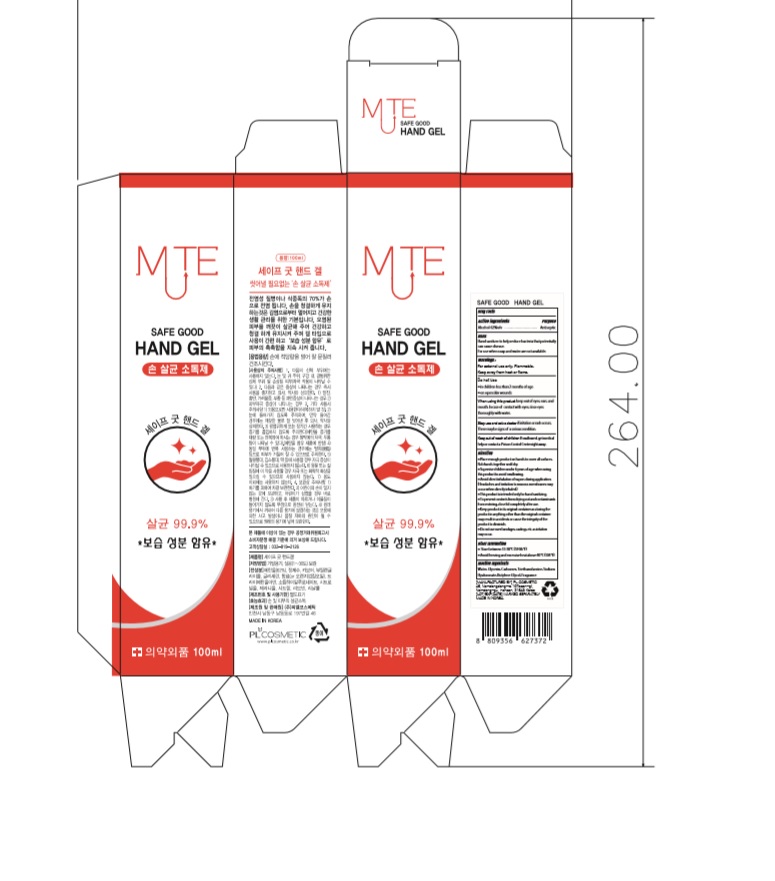 DRUG LABEL: SAFE GOOD HAND Gel
NDC: 74339-9162 | Form: GEL
Manufacturer: PL COSMETIC
Category: otc | Type: HUMAN OTC DRUG LABEL
Date: 20200406

ACTIVE INGREDIENTS: ALCOHOL 62 mL/100 mL
INACTIVE INGREDIENTS: GLYCERIN; CARBOMER HOMOPOLYMER, UNSPECIFIED TYPE; WATER; BUTYLENE GLYCOL; HYALURONATE SODIUM; TROLAMINE

[WITH OUTER BOX SAFE GOOD HAND Gel] 100 ml : 74339-9162